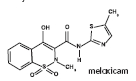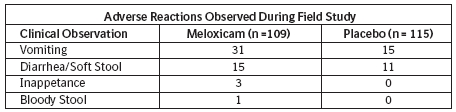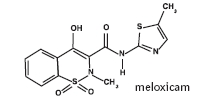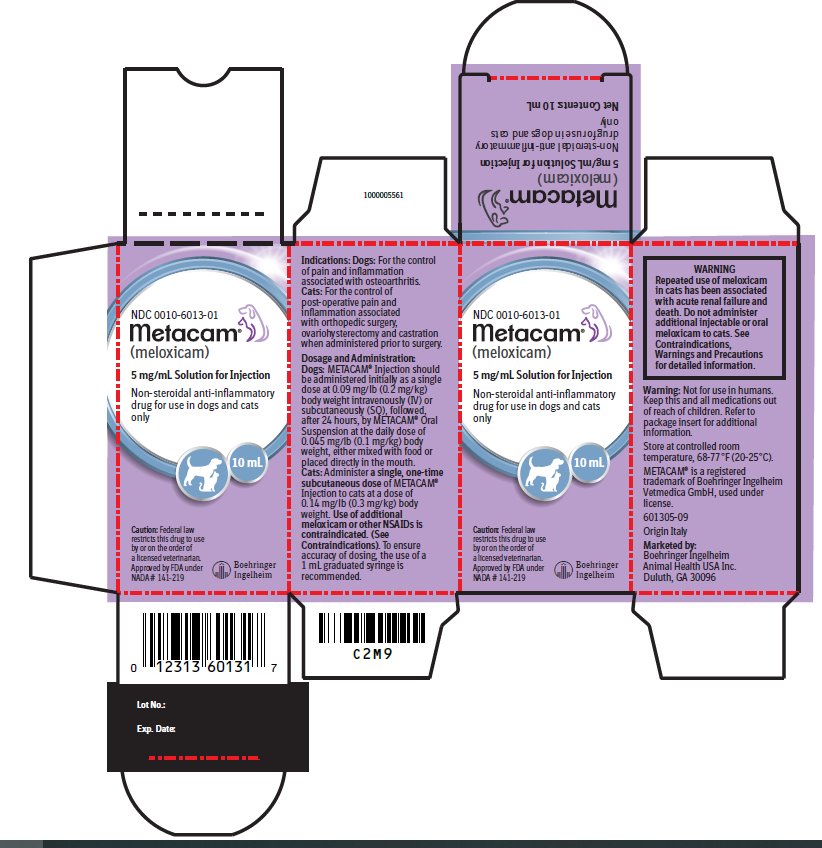 DRUG LABEL: Metacam
NDC: 0010-6013 | Form: INJECTION, SOLUTION
Manufacturer: Boehringer Ingelheim Animal Health USA Inc.
Category: animal | Type: PRESCRIPTION ANIMAL DRUG LABEL
Date: 20250123

ACTIVE INGREDIENTS: MELOXICAM 5 mg/1 mL
INACTIVE INGREDIENTS: MEGLUMINE 3.125 mg/1 mL; POLOXAMER 188 50 mg/1 mL; SODIUM CHLORIDE 6.0 mg/1 mL; GLYCINE 5.0 mg/1 mL; ALCOHOL 150 mg/1 mL; GLYCOFUROL 100 mg/1 mL

Metacam®
(meloxicam)
5 mg/mL Solution for Injection

Package Insert for Dogs

Non-steroidal anti-inflammatory drug for use in dogs and cats only

Caution:

Federal law restricts this drug to use by or on the order of a licensed veterinarian.

BOXED WARNING

Warning: Repeated use of meloxicam in cats has been associated with acute renal failure and death. Do not administer additional injectable or oral meloxicam to cats. See Contraindications, Warnings, and Precautions for detailed information.

Description:

Meloxicam is a non-steroidal anti-inflammatory drug (NSAID) of the oxicam class. Each mL of this sterile product for injection contains meloxicam 5.0 mg, alcohol 15%, glycofurol 10%, poloxamer 188 5%, sodium chloride 0.6%, glycine 0.5% and meglumine 0.3%, in water for injection, pH adjusted with sodium hydroxide and hydrochloric acid.

Indications:

Dogs: METACAM Injection is indicated in dogs for the control of pain and inflammation associated with osteoarthritis.

Dosage and Administration:

Carefully consider the potential benefits and risk of METACAM and other treatment options before deciding to use METACAM. Use the lowest effective dose for the shortest duration consistent with individual response.

Dogs: METACAM Injection should be administered initially as a single dose at 0.09 mg/lb (0.2 mg/kg) body weight intravenously (IV) or subcutaneously (SQ), followed, after 24 hours, by METACAM Oral Suspension at the daily dose of 0.045 mg/lb (0.1 mg/kg) body weight, either mixed with food or placed directly in the mouth.

Contraindications:

Dogs with known hypersensitivity to meloxicam should not receive METACAM Injection.

Warnings:

Not for use in humans. Keep this and all medications out of reach of children. Consult a physician in case of accidental ingestion by humans. For IV or SQ injectable use in dogs. All dogs should undergo a thorough history and physical examination before administering any NSAID. Appropriate laboratory testing to establish hematological and serum biochemical baseline data is recommended prior to, and periodically during use of any NSAID in dogs.

Owner should be advised to observe their dogs for signs of potential drug toxicity.

Precautions:

The safe use of METACAM Injection in dogs younger than 6 months of age, dogs used for breeding, or in pregnant or lactating bitches has not been evaluated. Meloxicam is not recommended for use in dogs with bleeding disorders, as safety has not been established in dogs with these disorders. Safety has not been established for intramuscular (IM) administration in dogs. When administering METACAM Injection, use a syringe of appropriate size to ensure precise dosing. As a class, cyclo-oxygenase inhibitory NSAIDs may be associated with gastrointestinal, renal and hepatic toxicity. Sensitivity to drug-associated adverse events varies with the individual patient. Dogs that have experienced adverse reactions from one NSAID may experience adverse reactions from another NSAID. Patients at greatest risk for renal toxicity are those that are dehydrated, on concomitant diuretic therapy, or those with existing renal, cardiovascular, and/or hepatic dysfunction. Concurrent administration of potentially nephrotoxic drugs should be carefully approached. NSAIDs may inhibit the prostaglandins that maintain normal homeostatic function. Such anti-prostaglandin effects may result in clinically significant disease in patients with underlying or preexisting disease that has not been previously diagnosed.

Since NSAIDs possess the potential to induce gastrointestinal ulcerations and/or perforations, concomitant use with other anti-inflammatory drugs, such as NSAIDs or corticosteroids, should be avoided. If additional pain medication is needed after the administration of the total daily dose of METACAM Oral Suspension, a non-NSAID or noncorticosteroid class of analgesia should be considered. The use of another NSAID is not recommended. Consider appropriate washout times when switching from corticosteroid use or from one NSAID to another in dogs. The use of concomitantly protein-bound drugs with METACAM Injection has not been studied in dogs. Commonly used protein-bound drugs include cardiac, anticonvulsant and behavioral medications. The influence of concomitant drugs that may inhibit metabolism of METACAM Injection has not been evaluated. Drug compatibility should be monitored in patients requiring adjunctive therapy. The effect of cyclo-oxygenase inhibition and the potential for thromboembolic occurrence or a hypercoagulable state has not been studied.

Adverse Reactions:

Dogs: A field study involving 224 dogs was conducted. Based on the results of this study, GI abnormalities (vomiting, soft stools, diarrhea, and inappetance) were the most common adverse reactions associated with the administration of meloxicam. The following table lists adverse reactions and the numbers of dogs that experienced them during the study. Dogs may have experienced more than one episode of the adverse reaction during the study.

In foreign suspected adverse drug reaction (SADR) reporting, adverse reactions related to meloxicam administration included: auto-immune hemolytic anemia (1 dog), thrombocytopenia (1 dog), polyarthritis (1 dog), nursing puppy lethargy (1 dog), and pyoderma (1 dog).

Post-Approval Experience (Rev. 2009):

The following adverse reactions are based on post-approval adverse drug event reporting. The categories are listed in decreasing order of frequency by body system:

Gastrointestinal: vomiting, diarrhea, melena, gastrointestinal ulceration

Urinary: azotemia, elevated creatinine, renal failure

Neurological/Behavioral: lethargy, depression

Hepatic: elevated liver enzymes

Dermatologic: pruritus

Death has been reported as an outcome of the adverse events listed above. Acute renal failure and death have been associated with the use of meloxicam in cats.

To report suspected adverse drug events, for technical assistance or to obtain a copy of the SDS, contact Boehringer Ingelheim Animal Health USA Inc.,1-888-637-4251.

For additional information about adverse drug experience reporting for animal drugs, contact FDA at 1-888-FDA-VETS or online at www.fda.gov/reportanimalae.

Information For Dog Owners:

Meloxicam, like other NSAIDs, is not free from adverse reactions. Owners should be advised of the potential for adverse reactions and be informed of the clinical signs associated with NSAID intolerance. Adverse reactions may include vomiting, diarrhea, lethargy, decreased appetite and behavioral changes. Dog owners should be advised when their pet has received a meloxicam injection. Dog owners should contact their veterinarian immediately if possible adverse reactions are observed, and dog owners should be advised to discontinue METACAM therapy.

Clinical Pharmacology:

Meloxicam has nearly 100% bioavailability when administered orally or after subcutaneous injection in dogs. The terminal elimination half life after a single dose is estimated to be approximately 24 hrs (+/-30%) in dogs regardless of route of administration. Drug bioavailability, volume of distribution, and total systemic clearance remain constant up to 5 times the recommended dose for use in dogs. However, there is some evidence of enhanced drug accumulation and terminal elimination half-life prolongation when dogs are dosed for 45 days or longer.

Peak drug concentrations of 0.734 mcg/mL can be expected to occur within 2.5 hours following a 0.2 mg/kg subcutaneous injection in dogs. Based upon intravenous administration in Beagle dogs, the meloxicam volume of distribution in dogs (Vdλ) is approximately 0.32 L/kg and the total systemic clearance is 0.01 L/hr/kg. The drug is 97% bound to canine plasma proteins.

Effectiveness:

Dogs: The effectiveness of METACAM Injection was demonstrated in a field study involving a total of 224 dogs representing various breeds, all diagnosed with osteoarthritis. This placebo-controlled, masked study was conducted for 14 days. Dogs received a subcutaneous injection of 0.2 mg/kg METACAM Injection on day 1. The dogs were maintained on 0.1 mg/kg oral meloxicam from days 2 through 14. Variables evaluated by veterinarians included lameness, weight-bearing, pain on palpation, and overall improvement. Variables assessed by owners included mobility, ability to rise, limping, and overall improvement.

In this field study, dogs showed clinical improvement with statistical significance after 14 days of meloxicam treatment for all variables.

Animal Safety:

Dogs: 3 Day Target Animal Safety Study - In a three day safety study, METACAM Injection was administered intravenously to Beagle dogs at 1, 3, and 5 times the recommended dose (0.2, 0.6 and 1.0 mg/kg) for three consecutive days. Vomiting occurred in 1 of 6 dogs in the 5X group. Fecal occult blood was detected in 3 of 6 dogs in the 5X group. No clinically significant hematologic changes were seen, but serum chemistry changes were observed. Serum alkaline phosphatase (ALP) was significantly increased in one 1X dog and two of the 5X dogs. One dog in the 5X group had a steadily increasing GGT over 4 days, although the values remained within the reference range. Decreases in total protein and albumin occurred in 2 of 6 dogs in the 3X group and 3 of 6 dogs in the 5X group. Increases in blood urea nitrogen (BUN) occurred in 3 of 6 dogs in the 1X group, 2 of 6 dogs in the 3X group and 2 of 6 dogs in the 5X group. Increased creatinine occurred in 2 dogs in the 5X group. Increased urine protein excretion was noted in 2 of 6 dogs in the control group, 2 of 6 dogs in the 1X group, 2 of 6 dogs in the 3X group, and 5 of 6 dogs in the 5X group. Two dogs in the 5X group developed acute renal failure by Day 4. Bicarbonate levels were at or above normal levels in 1 of the 3X dogs and 2 of the 5X dogs.

Histological examination revealed gastrointestinal lesions ranging from superficial mucosal hemorrhages and congestion to erosions. Mesenteric lymphadenopathy was identified in 2 of 6 dogs in the 1X group, 4 of 6 dogs in the 3X group, and 5 of 6 dogs in the 5X group. Renal changes ranged from dilated medullary and cortical tubules and inflammation of the interstitium, to necrosis of the tip of the papilla in 2 of 6 dogs in the 1X group, 2 of 6 dogs in the 3X group, and 4 of 6 dogs in the 5X group.

Injection Site Tolerance - METACAM Injection was administered once subcutaneously to Beagle dogs at the recommended dose of 0.2 mg/kg and was well-tolerated by the dogs. Pain upon injection was observed in one of eight dogs treated with meloxicam. No pain or inflammation was observed post-injection. Long term use of METACAM Injection in dogs has not been evaluated.

Effect on Buccal Mucosal Bleeding Time (BMBT) - METACAM Injection (0.2 mg/kg) and placebo (0.4 mL/kg) were administered as single intravenous injections to 8 female and 16 male Beagle dogs. There was no statistically significant difference (p>0.05) in the average BMBT between the two groups.

Storage Information:

Store at controlled room temperature, 68-77°F (20-25°C). When used as labeled, there is no limit on the number of punctures throughout the full expiry period.

How Supplied:

METACAM 5 mg/mL Solution for Injection: 10 mL vial, NDC 0010-6013-01 – 10 mL

Approved by FDA under NADA # 141-219

Marketed by:
Boehringer Ingelheim Animal Health USA Inc.
Duluth, GA 30096

METACAM® is a registered trademark of Boehringer Ingelheim Vetmedica GmbH, used under license.

601307-10
Revised 11/2023
1000005563

Package Insert for Cats

5 mg/mL Solution for Injection

Non-steroidal anti-inflammatory drug for use in dogs and cats only

Caution:

Federal law restricts this drug to use by or on the order of a licensed veterinarian.

BOXED WARNING

Warning: Repeated use of meloxicam in cats has been associated with acute renal failure and death. Do not administer additional injectable or oral meloxicam to cats. See Contraindications, Warnings, and Precautions for detailed information.

Description:

Meloxicam is a non-steroidal anti-inflammatory drug (NSAID) of the oxicam class. Each mL of this sterile product for injection contains meloxicam 5.0 mg, alcohol 15%, glycofurol 10%, poloxamer 188 5%, sodium chloride 0.6%, glycine 0.5% and meglumine 0.3%, in water for injection, pH adjusted with sodium hydroxide and hydrochloric acid.

Indications:

Cats: For the control of postoperative pain and inflammation associated with orthopedic surgery, ovariohysterectomy and castration when administered prior to surgery.

Dosage and Administration:

Carefully consider the potential benefits and risk of METACAM and other treatment options before deciding to use METACAM. Use the lowest effective dose for the shortest duration consistent with individual response.

Cats: Administer a single, one-time subcutaneous dose of METACAM Injection to cats at a dose of 0.14 mg/lb (0.3 mg/kg) body weight. Use of additional meloxicam or other NSAIDs is contraindicated. (See Contraindications). To ensure accuracy of dosing, the use of a 1 mL graduated syringe is recommended.

Contraindications:

Cats with known hypersensitivity to meloxicam should not receive METACAM Injection. Additional doses of meloxicam or other NSAIDs in cats are contraindicated, as no safe dosage for repeated NSAID administration has been established (See Animal Safety). Do not use meloxicam in cats with pre-existing renal dysfunction.

Warnings:

Not for use in humans. Keep this and all medications out of reach of children. Consult a physician in case of accidental ingestion by humans. For subcutaneous (SQ) injectable use in cats. Do not use IV in cats.

Do not administer a second dose of meloxicam.

Do not follow the single, one-time dose of meloxicam with any other NSAID.

Do not administer METACAM Oral Suspension following the single, one-time injectable dose of meloxicam.

When administering any NSAID, appropriate laboratory testing to establish hematological and serum biochemical baseline data is recommended prior to use in dogs and cats. All cats should undergo a thorough history and physical examination before administering meloxicam. Do not repeat the single, one-time dose of meloxicam in cats.
Owner should be advised to observe their cats for signs of potential drug toxicity.

Precautions:

The safe use of METACAM Injection in cats younger than 4 months of age, cats used for breeding, or in pregnant or lactating queens has not been evaluated.

Meloxicam is not recommended for use in cats with bleeding disorders, as safety has not been established in cats with these disorders. Safety has not been established for intravenous (IV) or intramuscular (IM) use in cats. When administering METACAM Injection, use a syringe of appropriate size to ensure precise dosing.

As a class, cyclo-oxygenase inhibitory NSAIDs may be associated with gastrointestinal, renal, and hepatic toxicity. Sensitivity to drug-associated adverse events varies with the individual patient. Cats that have experienced adverse reactions from one NSAID may experience adverse reactions from another NSAID. NSAIDs may inhibit the prostaglandins that maintain normal homeostatic function. Such anti-prostaglandin effects may result in clinically significant disease in patients with underlying or pre-existing disease that has not been previously diagnosed.

Patients at greatest risk for adverse events are those that are dehydrated, on concomitant diuretic therapy, or those with existing renal, cardiovascular, and/or hepatic dysfunction. Concurrent administration of potentially nephrotoxic drugs should be carefully approached and monitored. Anesthetic drugs may affect renal perfusion; approach concomitant use of anesthetics and NSAIDs cautiously. Appropriate monitoring procedures should be employed during all surgical procedures. The use of perioperative parenteral fluids is recommended to decrease potential renal complications when using NSAIDs. If additional pain medication is needed after the single one-time dose of meloxicam, a non-NSAID class of analgesic may be necessary.

In one study^1, one cat in each NSAID treatment group had increased intraoperative hemorrhage.

Since NSAIDs possess the potential to induce gastrointestinal ulcerations and/or gastrointestinal perforation, concomitant use of meloxicam with other anti-inflammatory drugs, such as NSAIDs or corticosteroids, should be avoided.

Consider appropriate washout times when switching from corticosteroid use to meloxicam in cats. As a single use product in cats, meloxicam should not be followed by additional NSAIDs or corticosteroids.

The use of concomitantly protein-bound drugs with METACAM Injection has not been studied in cats. Commonly used protein-bound drugs include cardiac, anticonvulsant, and behavioral medications. The influence of concomitant drugs that may inhibit metabolism of METACAM Injection has not been evaluated. Drug compatibility should be monitored in patients requiring adjunctive therapy.

The effect of cyclo-oxygenase inhibition and the potential for thromboembolic occurrence or a hypercoagulable state has not been studied.

Adverse Reactions:

Cats: A field study involving 138 cats was conducted. Of the 72 cats receiving METACAM Injection, six cats (8.3%) experienced post-treatment elevated serum blood urea nitrogen (BUN) levels. The pre-treatment values were in the normal range. Of the 66 cats in the butorphanol treatment group, no cats experienced post-treatment elevated serum blood urea nitrogen levels. Nine cats (12.5%) receiving METACAM Injection had post-treatment anemia. Pre-treatment, these cats all had hematocrit and hemoglobin values in the normal range. Four cats (6.1%) in the butorphanol treatment group had post-treatment anemia. All but one cat, who had a mild anemia pre-treatment (hematocrit=21% and hemoglobin=7.0 g/dL) had normal pre-treatment values. Twenty-four hours after the injection with METACAM Injection, one cat experienced pain upon palpation of the injection site.

Foreign Experience:

Repeated use in cats has been associated with acute renal failure and death. In studies used for the foreign approval of METACAM Injection in cats, lethargy, vomiting, inappetance, and transient pain immediately after injection were noted. Diarrhea and fecal occult blood have also been reported.

Post-Approval Experience (Rev. 2009):

The following adverse reactions are based on post-approval adverse drug event reporting. The categories are listed in decreasing order of frequency by body system:

Urinary: azotemia, elevated creatinine, elevated phosphorus, renal failure

Gastrointestinal: anorexia, vomiting, diarrhea

Neurologic/Behavioral: lethargy, depression

Hematologic: anemia

Death has been reported as an outcome of the adverse events listed above. Acute renal failure and death have been associated with the use of meloxicam in cats.

To report suspected adverse drug events, for technical assistance or to obtain a copy of the SDS, contact Boehringer Ingelheim Animal Health USA Inc., 1-888-637-4251.

For additional information about adverse drug experience reporting for animal drugs, contact FDA at 1-888-FDA-VETS or online at www.fda.gov/reportanimalae.

Information For Cat Owners:

Meloxicam, like other NSAIDs, is not free from adverse reactions. Owners should be advised of the potential for adverse reactions and be informed of the clinical signs associated with NSAID intolerance. Adverse reactions may include vomiting, diarrhea, lethargy, decreased appetite and behavioral changes.

Cat owners should be advised when their pet has received a meloxicam injection. Cat owners should contact their veterinarian immediately if possible adverse reactions are observed.

Clinical Pharmacology:

Meloxicam has nearly 100% bioavailability after subcutaneous injection in cats. The terminal elimination half life after a single dose is estimated to be approximately 15 hrs (+/-10%) in cats. Peak drug concentrations of 1.1 mcg/mL can be expected to occur within 1.5 hours following a 0.3 mg/kg subcutaneous injection in cats. The volume of distribution (Vdλ) in cats is approximately 0.27 L/kg, with an estimated total systemic clearance of 0.013 L/hr/kg. The drug is 97% bound to feline plasma proteins.

Effectiveness:

Cats: The effectiveness of METACAM Injection was demonstrated in a masked field study involving a total of 138 cats representing various breeds. This study used butorphanol as an active control. Cats received either a single subcutaneous injection of 0.3 mg/kg METACAM Injection or 0.4 mg/kg butorphanol prior to onychectomy, either alone or in conjunction with surgical neutering. All cats were premedicated with acepromazine, induced with propofol and maintained on isoflurane. Pain assessment variables evaluated by veterinarians included additional pain intervention therapy, gait/lameness score, analgesia score, sedation score, general impression score, recovery score, and visual analog scale score. Additionally, a cumulative pain score, which was the summation of the analgesia, sedation, heart rate and respiratory rate scores was evaluated. A palpometer was used to quantify the pain threshold.

A substantial number of cats required additional intervention in the 0-24 hour postsurgical period, with the majority of these interventions taking place within the first hour. Therefore, the percentage of cats in each group that received one or more interventions was designated as the primary assessment variable. Approximately half of the cats in each group received a pain intervention as a result of the first (time 0) post-surgical evaluation, i.e., extubation. At this point, the need to provide a pain intervention was not statistically significant between the two groups (p=0.7215). However, the median number of interventions was one per cat in the meloxicam group and two per cat in the butorphanol group and this difference was statistically significant (p=0.0021). The statistical evaluation supports the conclusion that the meloxicam test article is non-inferior to the butorphanol active control. Forty-eight of the 72 cats in the meloxicam group received one or more interventions (66.7%), and 47 of 66 cats in the butorphanol group received one or more interventions (71.2%). The number of interventions administered to the meloxicam group was less than the butorphanol group at 1, 3, 5, 8, 12, and 24 hours post-surgery.

Cats receiving METACAM Injection showed improvement in the pain assessment variables.

Animal Safety:

Cats: 3 Day Target Animal Safety Study - In a three day safety study, subcutaneous METACAM Injection administration to healthy cats at up to 1.5 mg/kg (5X the recommended dose) resulted in vomiting in three cats (1 of 6 control cats and 2 of 6 cats in 5X) and loose stools in four cats (2 of 6 control cats and 2 of 6 cats in 5X). Fecal occult blood was detected in ten of the twenty four cats, including two cats in the control group. This was not a dose-related event.

Clinically significant hematologic changes seen included increased PT and APTT in two cats (1 of 6 control cats and 1 of 6 cats in 5X), and elevated white blood cell counts in cats having renal or GI tract lesions. Serum chemistry changes observed included decreased total protein in four of 24 cats (1 of 6 cats in 1X, 2 of 6 cats in 3X and 1 of 6 cats in 5X), concomitant increases in blood urea nitrogen (BUN) and creatinine values in 2 of 6 cats in 5X.

Histological examination revealed gastrointestinal lesions ranging from inflammatory cell infiltration of the mucosa of the GI tract to erosions. Mesenteric lymphadenopathy was identified in 1 of 6 cats in 1X. Renal changes ranged from dilated medullary (2 of 6 cats in 1X, 1 of 6 cats in 3X, and 1 of 6 cats in 5X) and cortical (3 of 6 cats in 1X, 1 of 6 cats in 3X, and 3 of 6 cats in 5X) tubules and inflammation (2 of 6 cats in 1X, 2 of 6 cats in 3X, and 2 of 6 cats in 5X) or fibrosis (2 of 6 cats in 3X and 2 of 6 cats in 5X) of the interstitium to necrosis of the tip of the papilla (5 of 6 cats in 5X).

Subsequent oral dosing - In a nine day study with three treatment groups, METACAM Injection was given as a single subcutaneous injection using doses of 0 mg/kg (saline injection), 0.3 mg/kg and 0.6 mg/kg on Day 0. METACAM Oral Suspension, 1.5 mg/mL or saline was then administered orally once-daily at the same respective dose (0.3 or 0.6 mg/kg) for eight consecutive days. Clinical adverse reactions included vomiting, diarrhea, lethargy, and decreased food consumption in the treated groups, and one day of diarrhea in one control cat. The gross necropsy report includes observation of reddened GI mucosa in 3 of 4 cats in the 0.3 mg/kg group and 1 of 4 cats in the 0.6 mg/kg group. All saline-treated cats were normal. By Day 9, one cat in both the 0.3 mg/kg group and the 0.6 mg/kg group died and another cat in the 0.3 mg/kg group was moribund. The cause of death for these cats could not be determined, although the pathologist reported pyloric/duodenal ulceration in the cats in 0.6 mg/kg group. The safety studies demonstrate a narrow margin of safety.

Injection Site Tolerance - Histopathology of the injection sites revealed hemorrhage and inflammation, myofiber atrophy, panniculitis, fibrin deposition, and fibroblast proliferation. These findings were present in cats in all groups, with the 3X cats having the most present. No safe repeat dose has been established in cats.

Storage Information:

Store at controlled room temperature, 68-77°F (20-25°C). When used as labeled, there is no limit on the number of punctures throughout the full expiry period.

How Supplied:

METACAM 5 mg/mL Solution for Injection: 10 mL vial, NDC 0010-6013-01 – 10 mL

Reference:

^1Slingsby L.S., A.E. Waterman-Pearson. Comparison between meloxicam and carprofen for postoperative analgesia after feline ovariohysterectomy. Jour of Small Anim Pract (2002)43:286-289.

Approved by FDA under NADA # 141-219

Marketed by:
Boehringer Ingelheim Animal Health USA Inc.
Duluth, GA 30096

METACAM® is a registered trademark of Boehringer Ingelheim Vetmedica GmbH, used under license.

601307-10
Revised 11/2023
1000005563